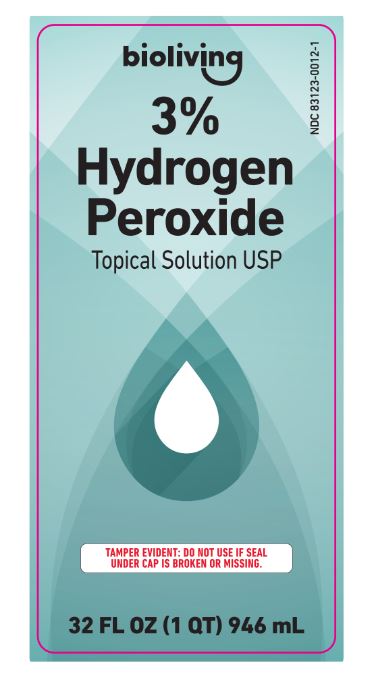 DRUG LABEL: HYDROGEN PEROXIDE
NDC: 83123-0012 | Form: LIQUID
Manufacturer: BROSANT GROUP LLC
Category: otc | Type: HUMAN OTC DRUG LABEL
Date: 20230116

ACTIVE INGREDIENTS: HYDROGEN PEROXIDE 3 mL/100 mL
INACTIVE INGREDIENTS: WATER 97 mL/100 mL

Active Ingredient

Hydrogen Peroxide 3%

Purpose

First aid antiseptic oral debriding agent

Uses

-first aid to help prevent the risk of infection in minor cuts, scrapes and burns

-aids in the removal of phlegm, mucus, or other secretions associated with occasional sore mouth

Warnings

For external use only

Do not use

-in the eyes or apply over large areas of the body

-longer than one week

Ask a doctor before use if you have

-deep puncture wounds, animal bites or serious burns

Stop use and ask a doctor if

-swelling, rash, or fever develops

-the condition persists or get worse

-sore mouth symptoms do not improve in 7 days

-irritation, pain, or redness persists or worsen

Keep out of reach of children

In case of ingestion, get medical help or contact a Poison Control Center (1-800-222-1222) right away

Directions

For use as a first aid antiseptic

-clean affected area

-if bandaged, let dry first

-apply small amount of product on affected area 1-3 times a day

-may be covered with a sterile bandage

For use as an oral debriding agent (oral rinse):

-adults and children 2 years of age and over:

-mix with and equal amount of water
-swish around in the mouth over affected area for at least 1 minute and then spit out. Do not swallow.

-use up 4 times daily after meals and at bedtime or as directed by a dentist or doctor

children under 12 years should be supervised in the use od this product

children under 2 years of age: consult a doctor or dentist

Other information

-keep tightly closed and in a dark place at room temperature

-do not shake botlle. Hold away from face when opening

Inactive ingredient

purified water

PACKAGE LABEL

bioliving

3% hydrogen peroxide

topical solution USP

Tamper evident: do not use if seal under cap is broken or missing

32 FL OZ (1 QT) 946 mL